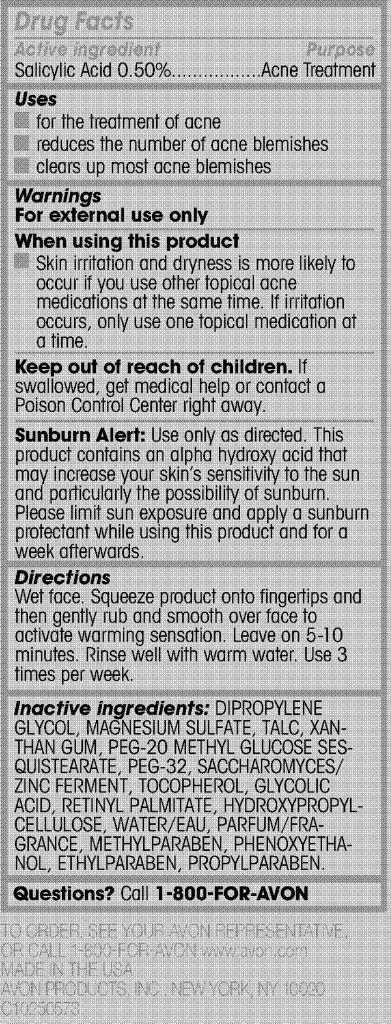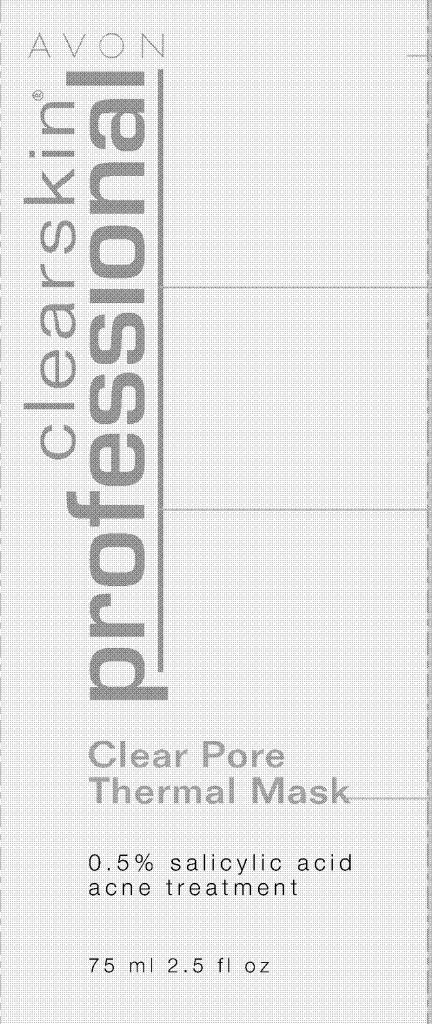 DRUG LABEL: Clearskin Professional
NDC: 10096-0226 | Form: GEL
Manufacturer: Avon Products, Inc.
Category: otc | Type: HUMAN OTC DRUG LABEL
Date: 20100917

ACTIVE INGREDIENTS: Salicylic acid 0.375 mL/75 mL
INACTIVE INGREDIENTS: DIPROPYLENE GLYCOL	; TALC	; XANTHAN GUM	; GLYCOLIC ACID	; WATER	; METHYLPARABEN	; PHENOXYETHANOL	; ETHYLPARABEN	; PROPYLPARABEN	

Drug Facts

Active ingredient
Salicylic Acid 0.50%.........

Purpose
.........Acne Treatment

Uses

- for the treatment of acne
- reduces the number of acne blemishes
- clears up most acne blemishes

Warnings
For external use only

When using this product

- Skin irritation and dryness is more likely tooccur if you use other topical acne medications at the same time. If irritation occurs, only use one topical medication at a time.

Keep out of reach of children. If
swallowed, get medical help or contact a
Poison Control Center right away.

PRECAUTIONS

Sunburn Alert: Use only as directed. This
product contains an alpha hydroxy acid that
may increase your skin’s sensitivity to the sun
and particularly the possibility of sunburn.
Please limit sun exposure and apply a sunburn
protectant while using this product and for a
week afterwards.

Directions
Wet face. Squeeze product onto fingertips and
then gently rub and smooth over face to
activate warming sensation. Leave on 5-10
minutes. Rinse well with warm water. Use 3
times per week.

Inactive ingredients: DIPROPYLENE
GLYCOL, MAGNESIUM SULFATE, TALC, XANTHAN
GUM, PEG-20 METHYL GLUCOSE SESQUISTEARATE,
PEG-32, SACCHAROMYCES/
ZINC FERMENT, TOCOPHEROL, GLYCOLIC
ACID, RETINYL PALMITATE, HYDROXYPROPYLCELLULOSE,
WATER/EAU, PARFUM/FRAGRANCE,
METHYLPARABEN, PHENOXYETHANOL,
ETHYLPARABEN, PROPYLPARABEN.

Questions? Call 1-800-FOR-AVON